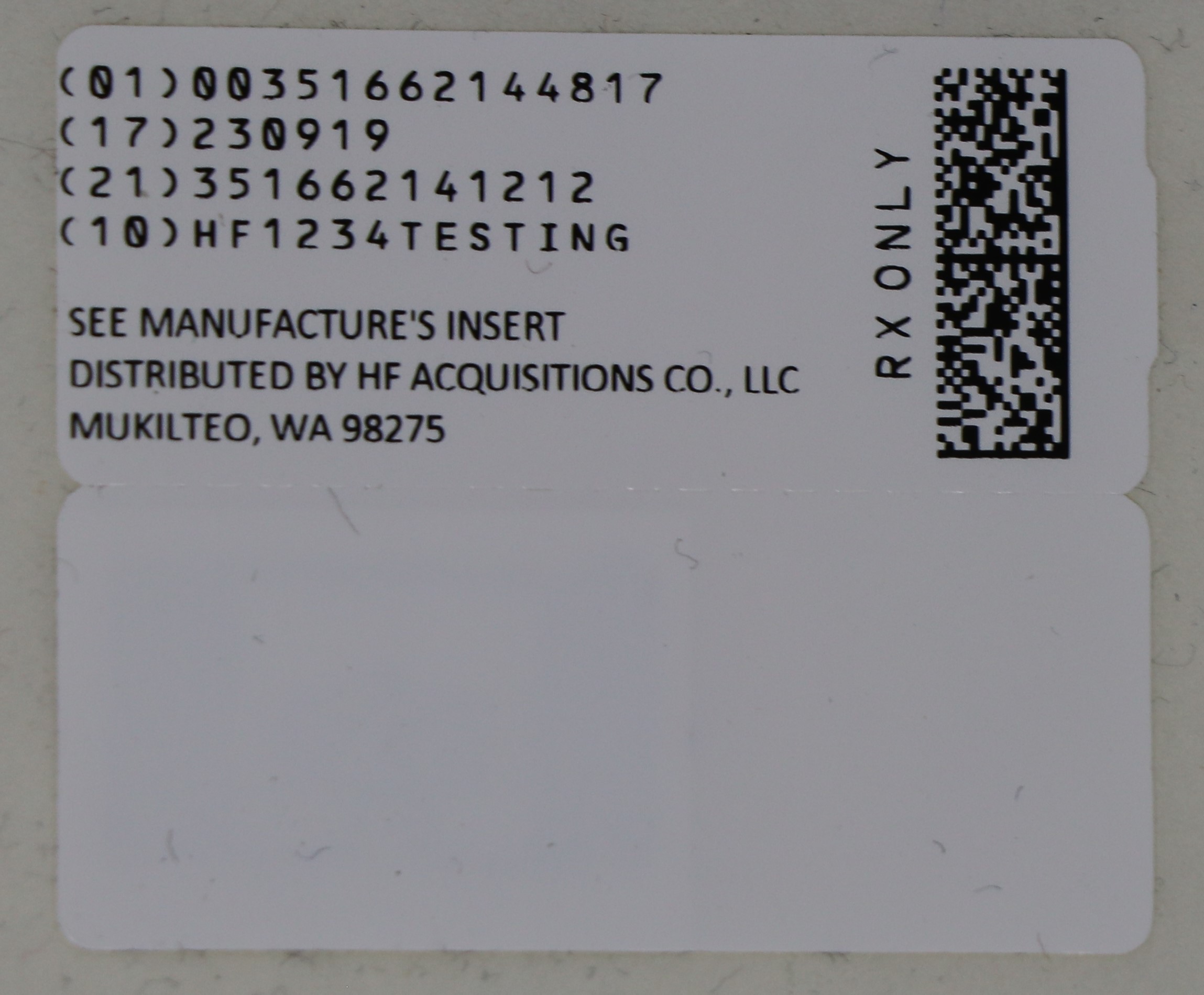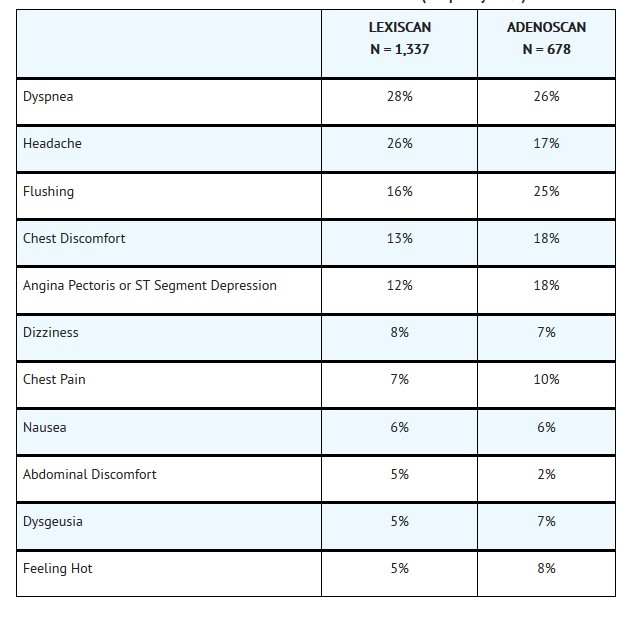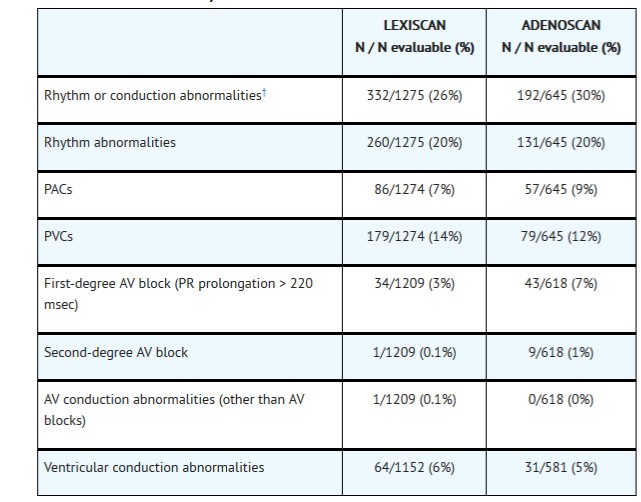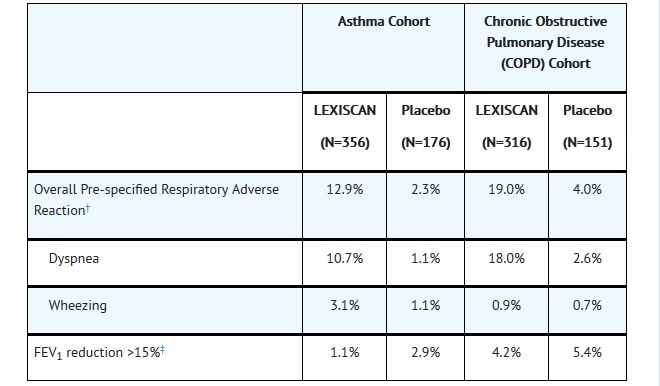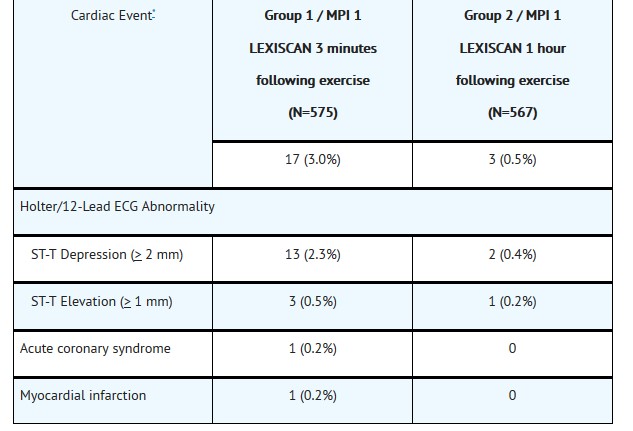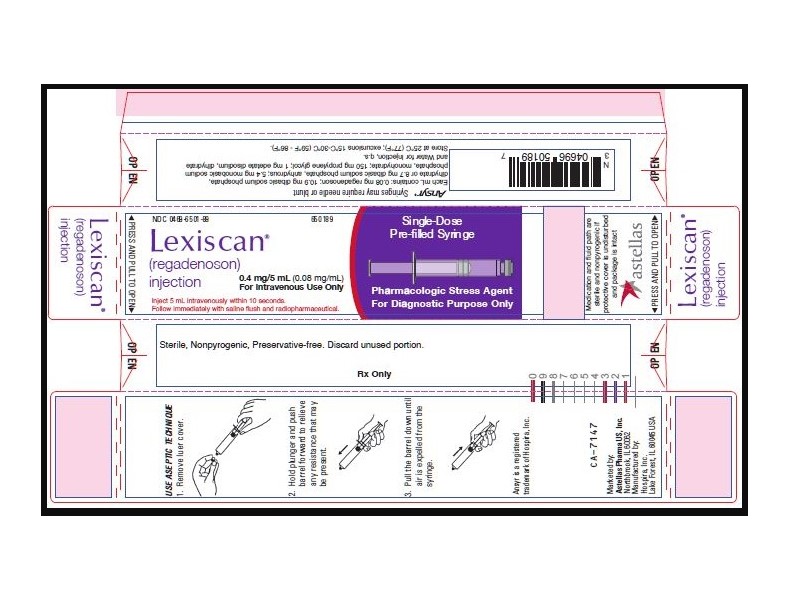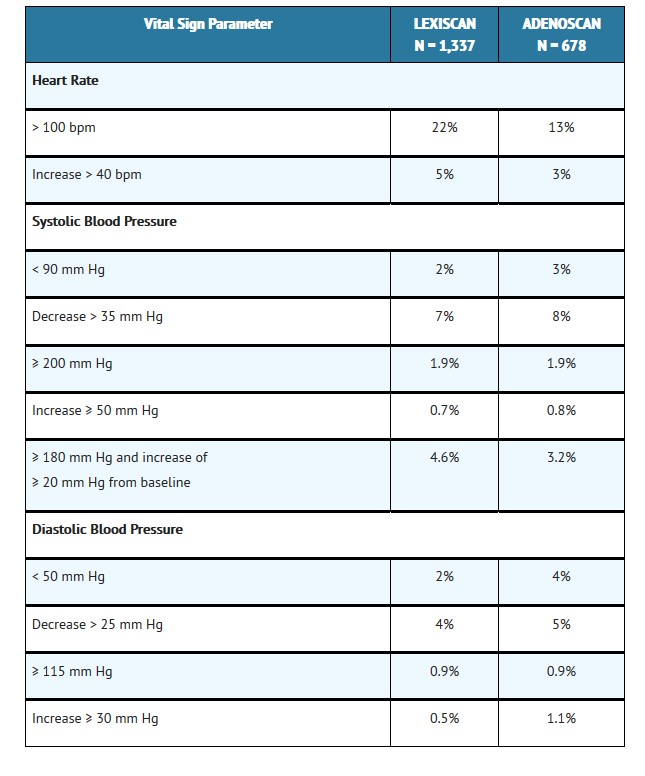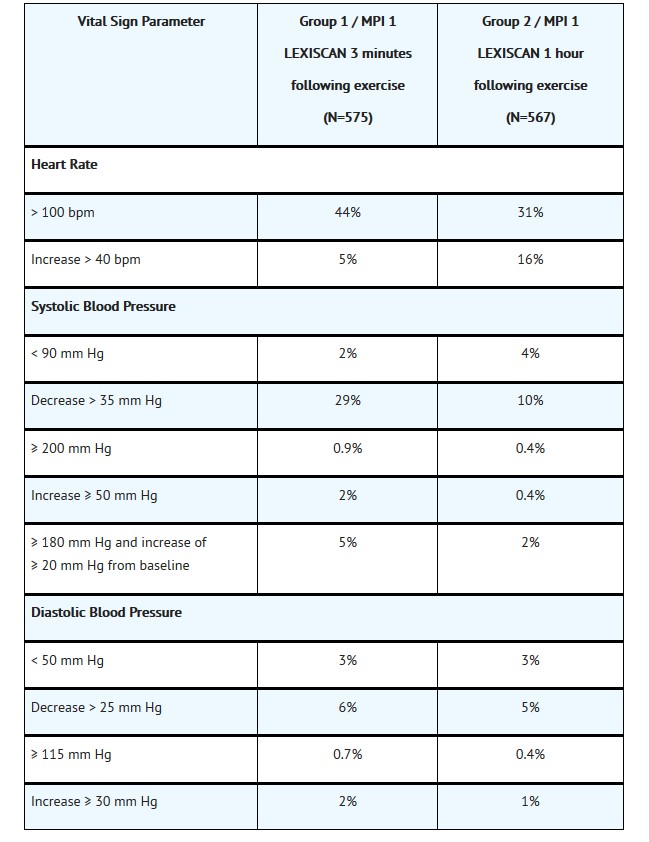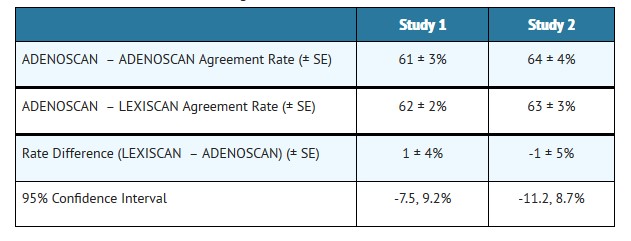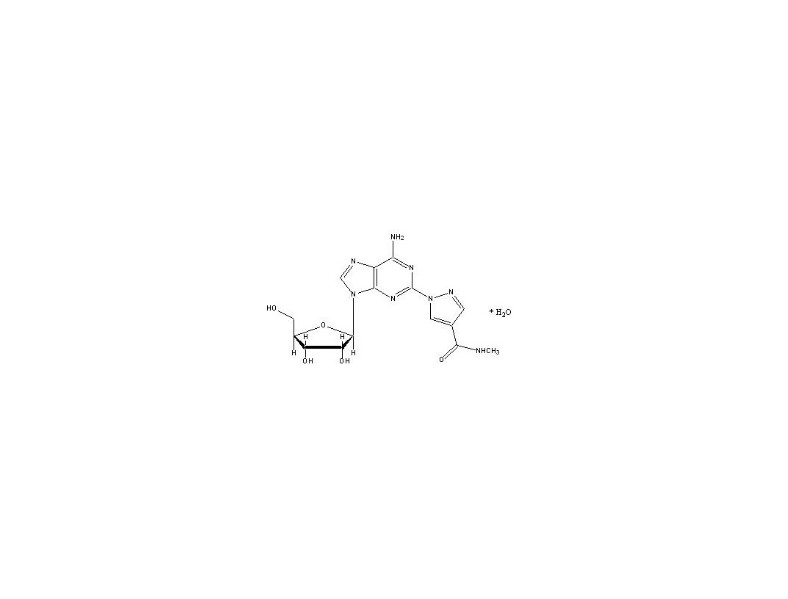 DRUG LABEL: LEXISCAN(R) (REGADENOSON)
NDC: 51662-1448 | Form: INJECTION, SOLUTION
Manufacturer: HF Acquisition Co LLC, DBA HealthFirst
Category: prescription | Type: HUMAN PRESCRIPTION DRUG LABEL
Date: 20240128

ACTIVE INGREDIENTS: REGADENOSON 0.08 mg/1 mL

LEXISCAN(R) (REGADENOSON) INJECTION 0.4mg/5mL (0.08 mg/mL) 5mL SYR

HIGHLIGHTS OR PRESCRIBING INFORMATION

These highlights do not include all the information needed to use LEXISCAN® safely and effectively. See full prescribing information for LEXISCAN®.
LEXISCAN® (regadenoson) injection for intravenous use
Initial U.S. Approval: 2008

RECENT MAJOR CHANGES

Dosage and Administration (2) 5/2018

Warnings and Precautions, Myocardial Ischemia (5-5.1) 5/2018

INDICATIONS AND USAGE

LEXISCAN® is a pharmacologic stress agent indicated for radionuclide myocardial perfusion imaging (MPI) in patients unable to undergo adequate exercise stress (1).

DOSAGE AND ADMINISTRATION

•
The recommended dose of LEXISCAN is 5 mL (0.4 mg regadenoson) administered as an intravenous injection within 10 seconds; followed immediately by saline flush and radiopharmaceutical (2).

DOSAGE FORMS AND STRENGTHS

•
Injection: Single-dose pre-filled syringe: 0.4 mg/5 mL (0.08 mg/mL) (3).

CONTRAINDICATIONS

Do not administer LEXISCAN to patients with:

•
Second- or third-degree AV block, or
•
sinus node dysfunction

unless the patients have a functioning artificial pacemaker (4).

WARNINGS AND PRECAUTIONS

•
Myocardial Ischemia. Fatal cardiac events have occurred. Avoid use in patients with symptoms or signs of acute myocardial ischemia, for example unstable angina or cardiovascular instability, who may be at greater risk. Cardiac resuscitation equipment and trained staff should be available before administration (5-5.1).
•
Sinoatrial (SA) and Atrioventricular (AV) Nodal Block. Adenosine receptor agonists, including LEXISCAN, can depress the SA and AV nodes and may cause first-, second- or third-degree AV block, or sinus bradycardia (5-5.2).
•
Atrial Fibrillation/Atrial Flutter. New-onset or recurrent atrial fibrillation with rapid ventricular response and atrial flutter have been reported (5-5.3).
•
Hypersensitivity, including anaphylaxis, angioedema, cardiac or respiratory arrest, respiratory distress, decreased oxygen saturation, hypotension, throat tightness, urticaria, and rashes have occurred. Have personnel and resuscitative equipment immediately available (5-5.4).
•
Hypotension. Adenosine receptor agonists, including LEXISCAN, induce vasodilation and hypotension. The risk of serious hypotension may be higher in patients with autonomic dysfunction, stenotic valvular heart disease, pericarditis or pericardial effusions, stenotic carotid artery disease with cerebrovascular insufficiency, or hypovolemia (5-5.5).
•
Hypertension. Adenosine receptor agonists, including LEXISCAN, may induce clinically significant increases in blood pressure particularly in patients with a history of hypertension and when the MPI includes low level exercise (5-5.6).
•
Bronchoconstriction. Adenosine receptor agonists, including LEXISCAN, may induce dyspnea, bronchoconstriction and respiratory compromise in patients with chronic obstructive pulmonary disease (COPD) or asthma. Resuscitative measures should be available (5-5.7).
•
Seizure. LEXISCAN may lower the seizure threshold. New onset or recurrence of convulsive seizures has occurred. Some seizures are prolonged and require urgent anticonvulsive management. Methylxanthine use is not recommended in patients who experience a seizure in association with LEXISCAN (5-5.8).
•
Cerebrovascular Accident (Stroke). Hemorrhagic and ischemic cerebrovascular accidents have occurred (5-5.9).

ADVERSE REACTIONS

The most common (incidence ≥ 5%) adverse reactions to LEXISCAN are dyspnea, headache, flushing, chest discomfort, dizziness, angina pectoris, chest pain, and nausea (6).

To report SUSPECTED ADVERSE REACTIONS, contact Astellas Pharma US, Inc. at 1-800-727-7003 or FDA at 1-800-FDA-1088 or www.fda.gov/medwatch.

DRUG INTERACTIONS

•
Methylxanthines, e.g., caffeine, aminophylline and theophylline, interfere with the activity of LEXISCAN (7-7.1, 12-12.2).
•
Aminophylline may be used to attenuate severe and/or persistent adverse reactions to LEXISCAN (7-7.1, 10).
•
Dipyridamole may increase the activity of LEXISCAN. When possible, withhold dipyridamole for at least two days prior to LEXISCAN administration (7-7.1).

See 17 for PATIENT COUNSELING INFORMATION.

Revised: 5/2018

1 INDICATIONS & USAGE

LEXISCAN® (regadenoson) injection is a pharmacologic stress agent indicated for radionuclide myocardial perfusion imaging (MPI) in patients unable to undergo adequate exercise stress.

2 DOSAGE AND ADMINISTRATION

The recommended dose of LEXISCAN is 5 mL (0.4 mg regadenoson) administered as an intravenous injection within 10 seconds.

•
Patients should be instructed to avoid consumption of any products containing methylxanthines, including caffeinated coffee, tea or other caffeinated beverages, caffeine-containing drug products, aminophylline and theophylline for at least 12 hours before a scheduled radionuclide MPI [see Drug Interactions (7-7.1) and Clinical Pharmacology (12-12.2)].
•
Parenteral drug products should be inspected visually for particulate matter and discoloration prior to administration, whenever solution and container permit. Do not administer LEXISCAN if it contains particulate matter or is discolored.
•
Administer LEXISCAN as an intravenous injection within 10 seconds into a peripheral vein using a 22 gauge or larger catheter or needle.
•
Administer a 5 mL saline flush immediately after the injection of LEXISCAN.
•
Administer the radionuclide myocardial perfusion imaging agent 10–20 seconds after the saline flush. The radionuclide may be injected directly into the same catheter as LEXISCAN.

3 DOSAGE FORMS & STRENGTHS

Single-dose pre-filled syringe: clear, colorless solution containing regadenoson 0.4 mg/5 mL (0.08 mg/mL).

4 CONTRAINDICATIONS

Do not administer LEXISCAN to patients with:

•
Second- or third-degree AV block, or
•
sinus node dysfunction

unless these patients have a functioning artificial pacemaker [see Warnings and Precautions (5-5.2)].

5 WARNINGS AND PRECAUTIONS

5.1 Myocardial Ischemia

Fatal and nonfatal myocardial infarction (MI), ventricular arrhythmias, and cardiac arrest have occurred following LEXISCAN injection. Avoid use in patients with symptoms or signs of acute myocardial ischemia, for example unstable angina or cardiovascular instability; these patients may be at greater risk of serious cardiovascular reactions to LEXISCAN. Cardiac resuscitation equipment and trained staff should be available before administering LEXISCAN. Adhere to the recommended duration of injection [see Dosage and Administration (2)]. As noted in an animal study, longer injection times may increase the duration and magnitude of increase in coronary blood flow [see Clinical Pharmacology (12-12.2)]. If serious reactions to LEXISCAN occur, consider the use of aminophylline, an adenosine antagonist, to shorten the duration of increased coronary blood flow induced by LEXISCAN [see Overdosage (10)].

5.2 Sinoatrial and Atrioventricular Nodal Block

Adenosine receptor agonists, including LEXISCAN, can depress the SA and AV nodes and may cause first-, second- or third-degree AV block, or sinus bradycardia requiring intervention. In clinical trials first-degree AV block (PR prolongation > 220 msec) developed in 3% of patients within 2 hours of LEXISCAN administration; transient second-degree AV block with one dropped beat was observed in one patient receiving LEXISCAN. In post-marketing experience, third-degree heart block and asystole within minutes of LEXISCAN administration have occurred [see Adverse Reactions (6-6.2)].

5.3 Atrial Fibrillation/Atrial Flutter

New-onset or recurrent atrial fibrillation with rapid ventricular response and atrial flutter have been reported following LEXISCAN injection [see Adverse Reactions (6-6.2)].

5.4 Hypersensitivity, Including Anaphylaxis

Anaphylaxis, angioedema, cardiac or respiratory arrest, respiratory distress, decreased oxygen saturation, hypotension, throat tightness, urticaria and rashes have occurred. In clinical trials, hypersensitivity reactions were reported in fewer than 1 percent of patients [see Adverse Reactions (6.1)]. Have personnel and resuscitative equipment immediately available.

5.5 Hypotension

Adenosine receptor agonists, including LEXISCAN, induce arterial vasodilation and hypotension. In clinical trials, decreased systolic blood pressure (> 35 mm Hg) was observed in 7% of patients and decreased diastolic blood pressure (> 25 mm Hg) was observed in 4% of patients within 45 minutes of LEXISCAN administration. The risk of serious hypotension may be higher in patients with autonomic dysfunction, hypovolemia, left main coronary artery stenosis, stenotic valvular heart disease, pericarditis or pericardial effusions, or stenotic carotid artery disease with cerebrovascular insufficiency. In post-marketing experience, syncope, transient ischemic attacks and seizures have been observed [see Adverse Reactions (6-6.2)].

5.6 Hypertension

Administration of adenosine receptor agonists, including LEXISCAN, may result in clinically significant increases in blood pressure in some patients. Among patients who experienced an increase in blood pressure in clinical trials, the increase was observed within minutes of LEXISCAN administration. Most increases resolved within 10 to 15 minutes, but in some cases, increases were observed at 45 minutes following administration [see Clinical Pharmacology (12-12.2)]. In post-marketing experience, cases of potentially clinically significant hypertension have been reported, particularly with underlying hypertension and when low-level exercise was included in the MPI [see Adverse Reactions (6-6.2)].

5.7 Bronchoconstriction

Adenosine receptor agonists, including LEXISCAN, may cause dyspnea, bronchoconstriction, and respiratory compromise. Appropriate bronchodilator therapy and resuscitative measures should be available prior to and following LEXISCAN administration [see Adverse Reactions (6-6.1), Clinical Pharmacology (12-12.2), Overdosage (10) and Patient Counseling Information (17)].

5.8 Seizure

LEXISCAN may lower the seizure threshold; obtain a seizure history. New-onset or recurrence of convulsive seizures has occurred following LEXISCAN injection. Some seizures are prolonged and require emergent anticonvulsive management. Aminophylline may increase the risk of seizures associated with LEXISCAN injection. Methylxanthine use is not recommended in patients who experience a seizure in association with LEXISCAN administration.

5.9 Cerebrovascular Accident (Stroke)

Hemorrhagic and ischemic cerebrovascular accidents have occurred. Hemodynamic effects of LEXISCAN including hypotension or hypertension may be associated with these adverse reactions [see Warnings and Precautions (5-5.5) and (5-5.6)].

6 ADVERSE REACTIONS

The following adverse reactions are discussed in more detail in other sections of the labeling.

•
Myocardial Ischemia [see Warnings and Precautions (5-5.1)]
•
Sinoatrial and Atrioventricular Nodal Block [see Warnings and Precautions (5-5.2)]
•
Atrial Fibrillation/Atrial Flutter [see Warnings and Precautions (5-5.3)]
•
Hypersensitivity, Including Anaphylaxis [see Warnings and Precautions (5-5.4)]
•
Hypotension [see Warnings and Precautions (5-5.5)]
•
Hypertension [see Warnings and Precautions (5-5.6)]
•
Bronchoconstriction [see Warnings and Precautions (5-5.7)]
•
Seizure [see Warnings and Precautions (5-5.8)]
•
Cerebrovascular Accident (Stroke) [see Warnings and Precautions (5-5.9)]

6.1 Clinical Trials Experience

Because clinical trials are conducted under widely varying conditions, adverse reaction rates observed in the clinical trials of a drug cannot be directly compared to rates in the clinical trials of another drug and may not reflect the rates observed in practice.

During clinical development, 1,651 patients were exposed to LEXISCAN, with most receiving 0.4 mg as a rapid (≤ 10 seconds) intravenous injection. Most of these patients received LEXISCAN in two clinical studies that enrolled patients who had no history of bronchospastic lung disease as well as no history of a cardiac conduction block of greater than first-degree AV block, except for patients with functioning artificial pacemakers. In these studies (Studies 1 and 2), 2,015 patients underwent myocardial perfusion imaging after administration of LEXISCAN (N = 1,337) or ADENOSCAN (N = 678). The population was 26–93 years of age (median 66 years), 70% male and primarily Caucasian (76% Caucasian, 7% African American, 9% Hispanic, 5% Asian). Table 1 shows the most frequently reported adverse reactions.

Overall, any adverse reaction occurred at similar rates between the study groups (80% for the LEXISCAN group and 83% for the ADENOSCAN group). Aminophylline was used to treat the reactions in 3% of patients in the LEXISCAN group and 2% of patients in the ADENOSCAN group. Most adverse reactions began soon after dosing, and generally resolved within approximately 15 minutes, except for headache which resolved in most patients within 30 minutes.

Table 1 Adverse Reactions in Studies 1 and 2 Pooled (Frequency ≥ 5%)

ECG Abnormalities

The frequency of rhythm or conduction abnormalities following LEXISCAN or ADENOSCAN is shown in Table 2 [see Warnings and Precautions (5-5.2)].

Table 2 Rhythm or Conduction Abnormalities* in Studies 1 and 2

*
12-lead ECGs were recorded before and for up to 2 hours after dosing.
†
includes rhythm abnormalities (PACs, PVCs, atrial fibrillation/flutter, wandering atrial pacemaker, supraventricular or ventricular arrhythmia) or conduction abnormalities, including AV block.

Respiratory Abnormalities

In a randomized, placebo-controlled trial of 999 patients with asthma (n = 532) or stable chronic obstructive pulmonary disease (n = 467), the overall incidence of pre-specified respiratory adverse reactions was greater in the LEXISCAN group compared to the placebo group (p < 0.001). Most respiratory adverse reactions resolved without therapy; a few patients received aminophylline or a short-acting bronchodilator. No differences were observed between treatment arms in the reduction of >15% from baseline at two-hours in FEV1 (Table 3).

Table 3 Respiratory Adverse Effects*

*
All patients continued the use of their respiratory medications as prescribed prior to administration of LEXISCAN.
†
Patients may have reported more than one type of adverse reaction. Adverse reactions were collected up to 24 hours following drug administration. Pre-specified respiratory adverse reactions included dyspnea, wheezing, obstructive airway disorder, dyspnea exertional, and tachypnea.
‡
Change from baseline at 2 hours.

Renal Impairment

In a randomized, placebo-controlled trial of 504 patients (LEXISCAN n=334 and placebo n=170) with a diagnosis or risk factors for coronary artery disease and NKFK/DOQI Stage III or IV renal impairment (defined as GFR 15-59 mL/min/1.73 m2), no serious adverse events were reported through the 24-hour follow-up period.

Inadequate Exercise Stress

In an open-label, multi-center trial evaluating LEXISCAN administration following inadequate exercise stress, 1,147 patients were randomized into one of two groups. Each group underwent two LEXISCAN stress myocardial perfusion imaging (MPI) procedures. Group 1 received LEXISCAN 3 minutes following inadequate exercise in the first LEXISCAN stress (MPI 1). Group 2 rested 1 hour after inadequate exercise to allow hemodynamics to return to baseline prior to receiving LEXISCAN (MPI 1). Both groups returned for a second stress MPI 1-14 days later and received LEXISCAN without exercise (MPI 2).

The most common adverse reactions are similar in type and incidence to those in Table 1 above for both Groups. The timing of the administration of LEXISCAN following inadequate exercise did not alter the common adverse reaction profile.

Table 4 shows a comparison of cardiac events of interest for the two groups [see Warnings and Precautions (5-5.1)]. The cardiac events were numerically higher in Group 1.

Table 4 Cardiac Events of Interest in Inadequate Exercise Stress Study

*
A clinically significant cardiac event was defined as any of the following events found on the Holter ECG/12-lead ECG within one hour after regadenoson administration: ventricular arrhythmias (sustained ventricular tachycardia, ventricular fibrillation, Torsade de Pointes, ventricular flutter); ST-T depression (≥ 2 mm); ST-T elevation (≥ 1 mm); AV block (2:1 AV block, AV Mobitz I, AV Mobitz II, complete heart block); sinus arrest > 3 seconds in duration
Or
• a Treatment Emergent Adverse Event (TEAE) per the MedDRA SMQ (narrow Scope) for myocardial infarction
Or
• a TEAE preferred term (PT) of angina unstable within 24 hours of regadenoson administration.

6.2 Post-Marketing Experience

The following adverse reactions have been reported from worldwide marketing experience with regadenoson. Because these reactions are reported voluntarily from a population of uncertain size, it is not always possible to reliably estimate their frequency or establish a causal relationship to drug exposure.

Cardiovascular

Myocardial infarction, cardiac arrest, ventricular arrhythmias, supraventricular tachyarrhythmias including atrial fibrillation with rapid ventricular response (new-onset or recurrent), atrial flutter, heart block (including third-degree block), asystole, marked hypertension, symptomatic hypotension in association with transient ischemic attack, acute coronary syndrome (ACS), seizures and syncope [see Warnings and Precautions (5-5.1), (5-5.2), (5-5.3), (5-5.5), (5-5.6) and (5-5.8)] have been reported. Some events required intervention with fluids and/or aminophylline [see Overdosage (10)]. QTc prolongation shortly after LEXISCAN administration has been reported.

Central Nervous System

Tremor, seizure, transient ischemic attack, and cerebrovascular accident including intracranial hemorrhage [see Warnings and Precautions (5-5.8) and (5-5.9)].

Gastrointestinal

Abdominal pain, occasionally severe, has been reported a few minutes after LEXISCAN administration, in association with nausea, vomiting, or myalgias; administration of aminophylline, an adenosine antagonist, appeared to lessen the pain. Diarrhea and fecal incontinence have also been reported following LEXISCAN administration.

Hypersensitivity

Anaphylaxis, angioedema, cardiac or respiratory arrest, respiratory distress, decreased oxygen saturation, hypotension, throat tightness, urticaria, rashes have occurred and have required treatment including resuscitation [see Warnings and Precautions (5-5.4)].

Musculoskeletal

Musculoskeletal pain has occurred, typically 10-20 minutes after LEXISCAN administration; the pain was occasionally severe, localized in the arms and lower back and extended to the buttocks and lower legs bilaterally. Administration of aminophylline appeared to lessen the pain.

Respiratory

Respiratory arrest, dyspnea and wheezing have been reported following LEXISCAN administration.

7 DRUG INTERACTIONS

No formal pharmacokinetic drug interaction studies have been conducted with LEXISCAN.

7.1 Effects of Other Drugs on LEXISCAN

•
Methylxanthines (e.g., caffeine, aminophylline and theophylline) are non-specific adenosine receptor antagonists that interfere with the vasodilation activity of LEXISCAN [see Clinical Pharmacology (12-12.2) and Patient Counseling Information (17)]. Patients should avoid consumption of any products containing methylxanthines as well as any drugs containing theophylline or aminophylline for at least 12 hours before LEXISCAN administration. Aminophylline may be used to attenuate severe or persistent adverse reactions to LEXISCAN [see Overdosage (10)].
•
In clinical studies, LEXISCAN was administered to patients taking other cardioactive drugs (i.e., β-blockers, calcium channel blockers, ACE inhibitors, nitrates, cardiac glycosides, and angiotensin receptor blockers) without reported adverse reactions or apparent effects on efficacy.
•
Dipyridamole may change the effects of LEXISCAN. When possible, withhold dipyridamole for at least two days prior to LEXISCAN administration.

7.2 Effect of LEXISCAN on Other Drugs

Regadenoson does not inhibit the metabolism of substrates for CYP1A2, CYP2C8, CYP2C9, CYP2C19, CYP2D6, or CYP3A4 in human liver microsomes, indicating that it is unlikely to alter the pharmacokinetics of drugs metabolized by these cytochrome P450 enzymes.

8 USE IN SPECIFIC POPULATIONS

8.1 Pregnancy

Risk Summary

There are no available data on LEXISCAN use in pregnant women to inform a drug-associated risk. In animal reproduction studies, adverse developmental outcomes were observed with the administration of regadenoson to pregnant rats and rabbits during organogenesis only at doses that produced maternal toxicity (see Data).

In the U.S. general population, the estimated background risk of major birth defects and miscarriage in clinically recognized pregnancies is 2-4% and 15-20%, respectively.

Data

Animal Data

Reproductive studies in rats showed that regadenoson doses 10 and 20 times the maximum recommended human dose (MRHD) based on body surface area caused reduced fetal body weights and significant ossification delays in fore- and hind limb phalanges and metatarsals; maternal toxicity also occurred at these doses. Skeletal variations were increased in all treated groups. In rabbits, maternal toxicity occurred at regadenoson doses administered during organogenesis at 4 times the MRHD; however, there were no teratogenic effects in offspring at this dose. At higher doses, 12 and 20 times the MRHD, maternal toxicity occurred along with increased embryo-fetal loss and fetal malformations.

8.2 Lactation

Risk Summary

There is no information on the presence of regadenoson in human milk, the effects on the breastfed infant, or the effects on milk production. Because of the potential risk of serious cardiac reactions in the breastfed infant, advise the nursing mother to pump and discard breast milk for 10 hours after administration of LEXISCAN.

8.4 Pediatric Use

Safety and effectiveness in pediatric patients have not been established.

8.5 Geriatric Use

Of the 1,337 patients receiving LEXISCAN in Studies 1 and 2, 56% were 65 years of age and over and 24% were 75 years of age and over. Older patients (> 75 years of age) had a similar adverse event profile compared to younger patients (< 65 years of age), but had a higher incidence of hypotension (2% vs. ≤ 1%).

8.6 Renal Impairment

No dose adjustment is needed in patients with renal impairment including patients with end stage renal disease and/or dependent on dialysis [see Pharmacokinetics (12-12.3)].

10 OVERDOSAGE

LEXISCAN overdosage may result in serious reactions [see Warnings and Precautions (5)]. In a study of healthy volunteers, symptoms of flushing, dizziness and increased heart rate were assessed as intolerable at LEXISCAN doses greater than 0.02 mg/kg.

Aminophylline to Reverse Effects

Methylxanthines, such as caffeine, aminophylline, and theophylline, are competitive adenosine receptor antagonists and aminophylline has been used to terminate persistent pharmacodynamic effects. Aminophylline may be administered in doses ranging from 50 mg to 250 mg by slow intravenous injection (50 mg to 100 mg over 30–60 seconds). Methylxanthine use is not recommended in patients who experience a seizure in association with LEXISCAN administration [see Warnings and Precautions (5-5.8)].

11 DESCRIPTION

Regadenoson is an A2A adenosine receptor agonist that is a coronary vasodilator [see Clinical Pharmacology (12-12.1)]. Regadenoson is chemically described as adenosine, 2-[4-[(methylamino)carbonyl]-1H-pyrazol-1-yl]-, monohydrate. Its structural formula is:

The molecular formula for regadenoson is C15H18N8O5 • H2O and its molecular weight is 408.37.
LEXISCAN is a sterile, nonpyrogenic solution for intravenous injection. The solution is clear and colorless. Each 1 mL in the 5 mL pre-filled syringe contains 0.084 mg of regadenoson monohydrate, corresponding to 0.08 mg regadenoson on an anhydrous basis, 10.9 mg dibasic sodium phosphate dihydrate or 8.7 mg dibasic sodium phosphate anhydrous, 5.4 mg monobasic sodium phosphate monohydrate, 150 mg propylene glycol, 1 mg edetate disodium dihydrate, and Water for Injection, with pH between 6.3 and 7.7.

12 CLINICAL PHARMACOLOGY

12.1 Mechanism of Action

Regadenoson is a low affinity agonist (Ki ≈ 1.3 µM) for the A2A adenosine receptor, with at least 10-fold lower affinity for the A1 adenosine receptor (Ki > 16.5 µM), and weak, if any, affinity for the A2B and A3 adenosine receptors. Activation of the A2A adenosine receptor by regadenoson produces coronary vasodilation and increases coronary blood flow (CBF).

12.2 Pharmacodynamics

Coronary Blood Flow

LEXISCAN causes a rapid increase in CBF which is sustained for a short duration. In patients undergoing coronary catheterization, pulsed-wave Doppler ultrasonography was used to measure the average peak velocity (APV) of coronary blood flow before and up to 30 minutes after administration of regadenoson (0.4 mg, intravenously). Mean APV increased to greater than twice baseline by 30 seconds and decreased to less than twice the baseline level within 10 minutes [see Clinical Pharmacology (12.3)].

Myocardial uptake of the radiopharmaceutical is proportional to CBF. Because LEXISCAN increases blood flow in normal coronary arteries with little or no increase in stenotic arteries, LEXISCAN causes relatively less uptake of the radiopharmaceutical in vascular territories supplied by stenotic arteries. MPI intensity after LEXISCAN administration is therefore greater in areas perfused by normal relative to stenosed arteries.

Effect of duration of injection

A study in dogs compared the effects of intravenous injection of 2.5 μg/kg regadenoson (in 10 mL) over 10 seconds and 30 seconds on CBF. The duration of a two-fold increase in CBF was 97±14 seconds (n=6) and 221±20 seconds (n=4), respectively, for the 10 second and 30 second injections. The peak effects (i.e., maximal increase) on CBF after the 10 second and 30 second injections were 217±15% and 297±33% above baseline, respectively. The times to peak effect on CBF were 17±2 seconds and 27±6 seconds, respectively.

Effect of Aminophylline

Aminophylline (100 mg, administered by slow intravenous injection over 60 seconds) injected 1 minute after 0.4 mg LEXISCAN in patients undergoing cardiac catheterization, was shown to shorten the duration of the coronary blood flow response to LEXISCAN as measured by pulsed-wave Doppler ultrasonography [see Overdosage (10)].

Effect of Caffeine

Ingestion of caffeine decreases the ability to detect reversible ischemic defects. In a placebo-controlled, parallel group clinical study, patients with known or suspected myocardial ischemia received a baseline rest/stress MPI followed by a second stress MPI. Patients received caffeine or placebo 90 minutes before the second LEXISCAN stress MPI. Following caffeine administration (200 or 400 mg), the mean number of reversible defects identified was reduced by approximately 60%. This decrease was statistically significant [see Drug Interactions (7-7.1) and Patient Counseling Information (17)].

Hemodynamic Effects

In clinical studies, the majority of patients had an increase in heart rate and a decrease in blood pressure within 45 minutes after administration of LEXISCAN. Maximum hemodynamic changes after LEXISCAN and ADENOSCAN in Studies 1 and 2 are summarized in Table 5.

Table 5 Hemodynamic Effects in Studies 1 and 2

Hemodynamic Effects Following Inadequate Exercise

In a clinical study, LEXISCAN was administered for MPI following inadequate exercise stress. More patients with LEXISCAN administration three minutes following inadequate exercise stress had an increase in heart rate and a decrease in systolic blood pressure compared with LEXISCAN administered at rest. The changes were not associated with any clinically significant adverse reactions. Maximum hemodynamic changes are presented in Table 6.

Table 6 Hemodynamic Effects in Inadequate Exercise Stress Study

Respiratory Effects

The A2B and A3 adenosine receptors have been implicated in the pathophysiology of bronchoconstriction in susceptible individuals (i.e., asthmatics). In in vitro studies, regadenoson has not been shown to have appreciable binding affinity for the A2B and A3 adenosine receptors.

In a randomized, placebo-controlled clinical trial of 999 patients with a diagnosis, or risk factors for, coronary artery disease and concurrent asthma or COPD, the incidence of respiratory adverse reactions (dyspnea, wheezing) was greater with LEXISCAN compared to placebo. Moderate (2.5%) or severe (< 1%) respiratory reactions were observed more frequently in the LEXISCAN group compared to placebo [see Adverse Reactions (6-6.1)].

12.3 Pharmacokinetics

In healthy subjects, the regadenoson plasma concentration-time profile is multi-exponential in nature and best characterized by 3-compartment model. The maximal plasma concentration of regadenoson is achieved within 1 to 4 minutes after injection of LEXISCAN and parallels the onset of the pharmacodynamic response. The half-life of this initial phase is approximately 2 to 4 minutes. An intermediate phase follows, with a half-life on average of 30 minutes coinciding with loss of the pharmacodynamic effect. The terminal phase consists of a decline in plasma concentration with a half-life of approximately 2 hours [see Clinical Pharmacology (12-12.2)]. Within the dose range of 0.3–20 µg/kg in healthy subjects, clearance, terminal half-life or volume of distribution do not appear dependent upon the dose.

A population pharmacokinetic analysis including data from subjects and patients demonstrated that regadenoson clearance decreases in parallel with a reduction in creatinine clearance and clearance increases with increased body weight. Age, gender, and race have minimal effects on the pharmacokinetics of regadenoson.

Specific Populations

Renally Impaired Patients: The disposition of regadenoson was studied in 18 patients with various degrees of renal function and in 6 healthy subjects. With increasing renal impairment, from mild (CLcr 50 to < 80 mL/min) to moderate (CLcr 30 to < 50 mL/min) to severe renal impairment (CLcr < 30 mL/min), the fraction of regadenoson excreted unchanged in urine and the renal clearance decreased, resulting in increased elimination half-lives and AUC values compared to healthy subjects (CLcr ≥ 80 mL/min). However, the maximum observed plasma concentrations as well as volumes of distribution estimates were similar across the groups. The plasma concentration-time profiles were not significantly altered in the early stages after dosing when most pharmacologic effects are observed. No dose adjustment is needed in patients with renal impairment.

Patients with End Stage Renal Disease: The pharmacokinetics of regadenoson in patients on dialysis has not been assessed; however, in an in vitro study regadenoson was found to be dialyzable.

Hepatically Impaired Patients: The influence of hepatic impairment on the pharmacokinetics of regadenoson has not been evaluated. Because greater than 55% of the dose is excreted in the urine as unchanged drug and factors that decrease clearance do not affect the plasma concentration in the early stages after dosing when clinically meaningful pharmacologic effects are observed, no dose adjustment is needed in patients with hepatic impairment.

Geriatric Patients: Based on a population pharmacokinetic analysis, age has a minor influence on the pharmacokinetics of regadenoson. No dose adjustment is needed in elderly patients.

Metabolism

The metabolism of regadenoson is unknown in humans. Incubation with rat, dog, and human liver microsomes as well as human hepatocytes produced no detectable metabolites of regadenoson.

Excretion

In healthy volunteers, 57% of the regadenoson dose is excreted unchanged in the urine (range 19-77%), with an average plasma renal clearance around 450 mL/min, i.e., in excess of the glomerular filtration rate. This indicates that renal tubular secretion plays a role in regadenoson elimination.

13 NONCLINICAL TOXICOLOGY

13.1 Carcinogenesis, Mutagenesis, Impairment of Fertility

Regadenoson was negative in the Ames bacterial mutation assay, chromosomal aberration assay in Chinese hamster ovary (CHO) cells, and mouse bone marrow micronucleus assay.

Long-term animal studies have not been conducted to evaluate LEXISCAN's carcinogenic potential or potential effects on fertility.

13.2 Animal Toxicology and/or Pharmacology

Cardiomyopathy

Minimal cardiomyopathy (myocyte necrosis and inflammation) was observed in rats following single-dose administration of regadenoson. Increased incidence of minimal cardiomyopathy was observed on day 2 in males at doses of 0.08, 0.2 and 0.8 mg/kg (1/5, 2/5, and 5/5) and in females (2/5) at 0.8 mg/kg. In a separate study in male rats, the mean arterial pressure was decreased by 30 to 50% of baseline values for up to 90 minutes at regadenoson doses of 0.2 and 0.8 mg/kg, respectively. No cardiomyopathy was noted in rats sacrificed 15 days following single administration of regadenoson. The mechanism of the cardiomyopathy induced by regadenoson was not elucidated in this study but was associated with the hypotensive effects of regadenoson. Profound hypotension induced by vasoactive drugs is known to cause cardiomyopathy in rats.

Local Irritation

Intravenous administration of LEXISCAN to rabbits resulted in perivascular hemorrhage, vein vasculitis, inflammation, thrombosis and necrosis, with inflammation and thrombosis persisting through day 8 (last observation day). Perivascular administration of LEXISCAN to rabbits resulted in hemorrhage, inflammation, pustule formation and epidermal hyperplasia, which persisted through day 8 except for the hemorrhage which resolved. Subcutaneous administration of LEXISCAN to rabbits resulted in hemorrhage, acute inflammation, and necrosis; on day 8 muscle fiber regeneration was observed.

14 CLINICAL STUDIES

Agreement between LEXISCAN and ADENOSCAN

The efficacy and safety of LEXISCAN were determined relative to ADENOSCAN in two randomized, double-blind studies (Studies 1 and 2) in 2,015 patients with known or suspected coronary artery disease who were indicated for pharmacologic stress MPI. A total of 1,871 of these patients had images considered valid for the primary efficacy evaluation, including 1,294 (69%) men and 577 (31%) women with a median age of 66 years (range 26–93 years of age). Each patient received an initial stress scan using ADENOSCAN (6-minute infusion using a dose of 0.14 mg/kg/min, without exercise) with a radionuclide gated SPECT imaging protocol. After the initial scan, patients were randomized to either LEXISCAN or ADENOSCAN, and received a second stress scan with the same radionuclide imaging protocol as that used for the initial scan. The median time between scans was 7 days (range of 1–104 days).

The most common cardiovascular histories included hypertension (81%), CABG, PTCA or stenting (51%), angina (63%), and history of myocardial infarction (41%) or arrhythmia (33%); other medical history included diabetes (32%) and COPD (5%). Patients with a recent history of serious uncontrolled ventricular arrhythmia, myocardial infarction, or unstable angina, a history of greater than first-degree AV block, or with symptomatic bradycardia, sick sinus syndrome, or a heart transplant were excluded. A number of patients took cardioactive medications on the day of the scan, including β-blockers (18%), calcium channel blockers (9%), and nitrates (6%). In the pooled study population, 68% of patients had 0–1 segments showing reversible defects on the initial scan, 24% had 2–4 segments, and 9% had ≥ 5 segments.

Comparison of the images obtained with LEXISCAN to those obtained with ADENOSCAN was performed as follows. Using the 17-segment model, the number of segments showing a reversible perfusion defect was calculated for the initial ADENOSCAN study and for the randomized study obtained using LEXISCAN or ADENOSCAN. The agreement rate for the image obtained with LEXISCAN or ADENOSCAN relative to the initial ADENOSCAN image was calculated by determining how frequently the patients assigned to each initial ADENOSCAN category (0–1, 2–4, 5–17 reversible segments) were placed in the same category with the randomized scan. The agreement rates for LEXISCAN and ADENOSCAN were calculated as the average of the agreement rates across the three categories determined by the initial scan. Studies 1 and 2 each demonstrated that LEXISCAN is similar to ADENOSCAN in assessing the extent of reversible perfusion abnormalities (Table 7).

Table 7 Agreement Rates in Studies 1 and 2

Use of LEXISCAN in Patients with Inadequate Exercise Stress

The efficacy and safety of LEXISCAN administered 3 minutes (Group 1) or 1 hour (Group 2) following inadequate exercise stress were evaluated in an open-label randomized, multi-center, non-inferiority study. Adequate exercise was defined as ≥ 85% maximum predicted heart rate and ≥ 5 METS. SPECT MPI was performed 60-90 minutes after LEXISCAN administration in each group (MPI 1). Patients returned 1-14 days later to undergo a second stress MPI with LEXISCAN without exercise (MPI 2).

All patients were referred for evaluation of coronary artery disease. Of the 1,147 patients randomized, a total of 1,073 patients received LEXISCAN and had interpretable SPECT scans at all visits; 538 in Group 1 and 535 in Group 2. The median age of the patients was 62 years (range 28 to 90 years) and included 633 (59%) men and 440 (41%) women.

Images from MPI 1 and MPI 2 for the two groups were compared for presence or absence of perfusion defects. The level of agreement between the MPI 1 and the MPI 2 reads in Group 1 was similar to the level of agreement between MPI 1 and MPI 2 reads in Group 2. However, two patients receiving LEXISCAN 3 minutes following inadequate exercise experienced a serious cardiac adverse reaction. No serious cardiac adverse reactions occurred in patients receiving LEXISCAN 1 hour following inadequate exercise stress [see Adverse Reactions (6.1), Clinical Pharmacology (12-12.2)].

16 HOW SUPPLIED/STORAGE AND HANDLING

LEXISCAN(R) (REGADENOSON) INJECTION is supplied in the following dosage forms.
NDC 51662-1448-1
LEXISCAN(R) (REGADENOSON) INJECTION 0.4mg/5mL (0.08 mg/mL) 5mL SYR

HF Acquisition Co LLC, DBA HealthFirst
Mukilteo, WA 98275

Also supplied in the following manufacture supplied dosage forms

LEXISCAN is supplied as a sterile, preservative-free solution containing 0.08 mg/mL regadenoson in the following package:

•
Single-dose 5 mL pre-filled plastic Ansyr® syringes with luer-lock fitting
(NDC 0469-6501-89).

Store at controlled room temperature, 25°C (77°F); excursions permitted to 15° to 30°C (59°– 86°F).

17 PATIENT COUNSELING INFORMATION

Drug Interaction

Patients should be instructed to avoid consumption of any products containing methylxanthines, including caffeinated coffee, tea or other caffeinated beverages, caffeine-containing drug products, aminophylline and theophylline for at least 12 hours before a scheduled radionuclide MPI [see Warnings and Precautions (5-5.8) and Clinical Pharmacology (12-12.2)].

Cardiovascular

Advise patients that they may be at increased risk of fatal and nonfatal heart attacks, abnormal heart rhythms, cardiac arrest, significant increase or decrease in blood pressure, or cerebrovascular accidents (stroke) with the use of LEXISCAN [see Warnings and Precautions (5-5.1), (5-5.3), (5-5.5), (5-5.6) and (5-5.9)].

Hypersensitivity

Inform patients that allergic reactions have been reported with LEXISCAN. Advise patients how to recognize such a reaction and when to seek medical attention [see Warnings and Precautions (5-5.4)].

Respiratory

Advise patients with COPD or asthma about the need for administration of pre- and post-study bronchodilator therapy and to call their clinician if they experience any shortness of breath or difficulty breathing following an MPI study with LEXISCAN [see Warnings and Precautions (5-5.7)].

Seizures

Advise patients that they may be at increased risk of seizures. Question patients about a history of seizures [see Warnings and Precautions (5-5.8)].

Lactation

Advise a woman to pump and discard breast milk for 10 hours after LEXISCAN administration [see Use in Specific Populations (8-8.2)].

Marketed by:
Astellas Pharma US, Inc.
Northbrook, IL 60062

Syringes Manufactured by:
Hospira, Inc.
Lake Forest, IL 60045 USA

LEXISCAN® and ADENOSCAN® are registered trademarks of Astellas US LLC. All other trademarks and registered trademarks are the property of their respective owners.

229780-LEX